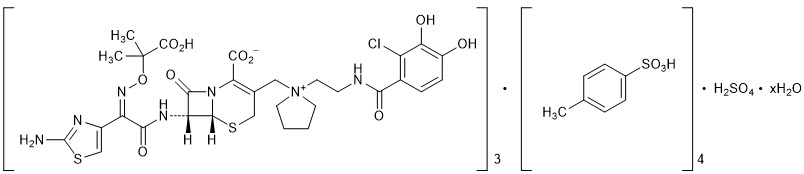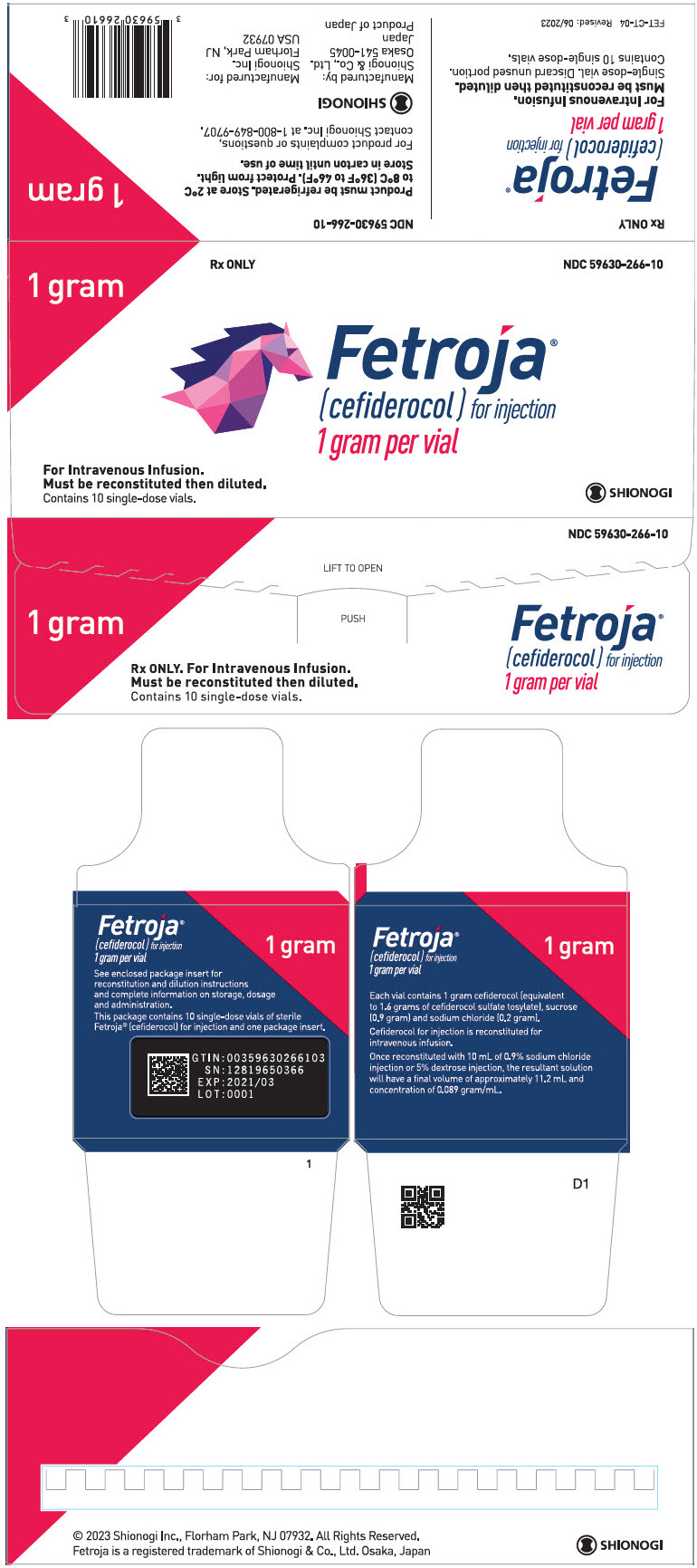 DRUG LABEL: Fetroja
NDC: 59630-266 | Form: INJECTION, POWDER, FOR SOLUTION
Manufacturer: Shionogi Inc.
Category: prescription | Type: HUMAN PRESCRIPTION DRUG LABEL
Date: 20250701

ACTIVE INGREDIENTS: CEFIDEROCOL SULFATE TOSYLATE 1 g/10 mL
INACTIVE INGREDIENTS: SUCROSE 900 mg/10 mL; SODIUM CHLORIDE 216 mg/10 mL; SODIUM HYDROXIDE; NITROGEN

HIGHLIGHTS OF PRESCRIBING INFORMATION

These highlights do not include all the information needed to use FETROJA ®safely and effectively. See full prescribing information for FETROJA.
FETROJA (cefiderocol) for injection, for intravenous use
Initial U.S. Approval: 2019

1 INDICATIONS AND USAGE

FETROJA is a cephalosporin antibacterial indicated in patients 18 years of age or older for the treatment of the following infections caused by susceptible Gram-negative microorganisms:

- Complicated Urinary Tract Infections (cUTI), including Pyelonephritis (1.1)
- Hospital-acquired Bacterial Pneumonia and Ventilator-associated Bacterial Pneumonia (HABP/VABP) (1.2)

To reduce the development of drug-resistant bacteria and maintain the effectiveness of FETROJA and other antibacterial drugs, FETROJA should be used only to treat or prevent infections that are proven or strongly suspected to be caused by bacteria. (1.3)

2 DOSAGE AND ADMINISTRATION

- Administer 2 grams of FETROJA for injection every 8 hours by intravenous (IV) infusion over 3 hours in patients with creatinine clearance (CLcr) 60 to 119 mL/min. (2.1)
- Dose adjustments are required for patients with CLcr less than 60 mL/min, (including patients receiving intermittent hemodialysis (HD) or continuous renal replacement therapy (CRRT)), and for patients with CLcr 120 mL/min or greater. (2.2)
- See full prescribing information for instructions on preparation of FETROJA doses. (2.3)
- See full prescribing information for drug compatibilities. (2.4)

3 DOSAGE FORMS AND STRENGTHS

For injection:1 gram of cefiderocol as a lyophilized powder for reconstitution in single-dose vials. (3)

4 CONTRAINDICATIONS

FETROJA is contraindicated in patients with a known history of severe hypersensitivity to cefiderocol and other beta-lactam antibacterial drugs or other components of FETROJA. (4)

5 WARNINGS AND PRECAUTIONS

- Increase in All-Cause Mortality in Patients with Carbapenem-Resistant Gram-Negative Bacterial Infections:An increase in all-cause mortality was observed in FETROJA-treated patients compared to those treated with best available therapy (BAT). Closely monitor the clinical response to therapy in patients with cUTI and HABP/VABP. (5.1)
- Hypersensitivity Reactions:Serious and occasionally fatal hypersensitivity (anaphylactic) reactions have been reported in patients receiving beta-lactam antibacterial drugs. Hypersensitivity was observed with FETROJA. Cross-hypersensitivity may occur in patients with a history of penicillin allergy. If an allergic reaction occurs, discontinue FETROJA. (5.2)
- Clostridioides difficile-associated Diarrhea (CDAD):CDAD has been reported with nearly all systemic antibacterial agents, including FETROJA. Evaluate if diarrhea occurs. (5.3)
- Seizures and Other Central Nervous System (CNS) Adverse Reactions:CNS adverse reactions such as seizures have been reported with FETROJA. If focal tremors, myoclonus, or seizures occur, evaluate patients to determine whether FETROJA should be discontinued. (5.4)

6 ADVERSE REACTIONS

- cUTI:The most frequently occurring adverse reactions in greater than or equal to 2% of cUTI patients treated with FETROJA were diarrhea, infusion site reactions, constipation, rash, candidiasis, cough, elevations in liver tests, headache, hypokalemia, nausea, and vomiting. (6.1)
- HABP/VABP:The most frequently occurring adverse reactions in greater than or equal to 4% of HABP/VABP patients treated with FETROJA were elevations in liver tests, hypokalemia, diarrhea, hypomagnesemia, and atrial fibrillation. (6.1)

To report SUSPECTED ADVERSE REACTIONS, contact Shionogi Inc. at 1-800-849-9707 or FDA at 1-800-FDA-1088 or www.fda.gov/medwatch.

7 DRUG INTERACTIONS

Use alternate testing methods to confirm positive results of dipstick tests (urine protein, ketones, or occult blood). (7.1)

FULL PRESCRIBING INFORMATION

1 INDICATIONS AND USAGE

1.1 Complicated Urinary Tract Infections (cUTIs), Including Pyelonephritis

FETROJA®is indicated in patients 18 years of age or older for the treatment of complicated urinary tract infections (cUTIs), including pyelonephritis caused by the following susceptible Gram-negative microorganisms: Escherichia coli, Klebsiella pneumoniae, Proteus mirabilis, Pseudomonas aeruginosa, and Enterobacter cloacaecomplex [see Clinical Studies (14.1)] .

1.2 Hospital-acquired Bacterial Pneumonia and Ventilator-associated Bacterial Pneumonia (HABP/VABP)

FETROJA is indicated in patients 18 years of age or older for the treatment of hospital-acquired bacterial pneumonia and ventilator-associated bacterial pneumonia, caused by the following susceptible Gram-negative microorganisms: Acinetobacter baumanniicomplex, Escherichiacoli, Enterobacter cloacaecomplex, Klebsiella pneumoniae, Pseudomonas aeruginosa, and Serratia marcescens [see Clinical Studies (14.2)].

1.3 Usage

To reduce the development of drug-resistant bacteria and maintain the effectiveness of FETROJA and other antibacterial drugs, FETROJA should be used only to treat or prevent infections that are proven or strongly suspected to be caused by susceptible bacteria. When culture and susceptibility information are available, they should be considered in selecting or modifying antibacterial therapy. In the absence of such data, local epidemiology and susceptibility patterns may contribute to the empiric selection of therapy.

2 DOSAGE AND ADMINISTRATION

2.1 Recommended Dosage

The recommended dosage of FETROJA is 2 grams administered every 8 hours by intravenous (IV) infusion over 3 hours in adults with a creatinine clearance (CLcr) of 60 to 119 mL/min.

Dosage adjustment of FETROJA is recommended for patients with CLcr less than 60 mL/min, including patients receiving intermittent hemodialysis (HD) or continuous renal replacement therapy (CRRT), and for patients with CLcr 120 mL/min or greater [see Dosage and Administration (2.2)]. The recommended duration of treatment with FETROJA is 7 to 14 days. The duration of therapy should be guided by the patient's clinical status.

2.2 Dosage Adjustments in Patients with CLcr Less Than 60 mL/min (Including Patients Undergoing Intermittent HD or CRRT), and CLcr 120 mL/min or Greater

Dosage Adjustments in Patients with CLcr Less Than 60 mL/min Including Patients Receiving Intermittent HD

Dosage adjustment of FETROJA is recommended in patients with CLcr less than 60 mL/min (Table 1). For patients undergoing intermittent HD, start the dosing of FETROJA immediately after the completion of HD. For patients with fluctuating renal function, monitor CLcr and adjust dosage accordingly.

Table 1 Recommended Dosage of FETROJA for Patients with CLcr Less Than 60 mL/min Including Patients Receiving Intermittent HD
Estimated Creatinine Clearance (CLcr) [CLcr = creatinine clearance estimated by Cockcroft-Gault equation.] | Dose | Frequency | Infusion Time
CLcr 30 to 59 mL/min | 1.5 grams | Every 8 hours | 3 hours
CLcr 15 to 29 mL/min | 1 gram | Every 8 hours | 3 hours
CLcr less than 15 mL/min, with or without intermittent HD [Cefiderocol is removed by HD; administer FETROJA immediately after HD for patients receiving intermittent HD.] | 0.75 grams | Every 12 hours | 3 hours
HD = hemodialysis.

Dosage Adjustments in Patients Receiving CRRT

For patients receiving CRRT, including continuous venovenous hemofiltration (CVVH), continuous venovenous hemodialysis (CVVHD), and continuous venovenous hemodiafiltration (CVVHDF), the dosage of FETROJA should be based on the effluent flow rate in CRRT (see Table 2). These recommendations are intended to provide initial dosing in patients receiving CRRT. Dosing regimens may need to be tailored based on residual renal function and patient's clinical status [see Use in Specific Populations (8.6)] .

Table 2 Recommended Dosage of FETROJA for Patients Receiving CRRT
Effluent Flow Rate [Ultrafiltrate flow rate for CVVH, dialysis flow rate for CVVHD, ultrafiltrate flow rate plus dialysis flow rate for CVVHDF.] | Recommended Dosage of FETROJA
2 L/hr or less | 1.5 grams every 12 hours
2.1 to 3 L/hr | 2 grams every 12 hours
3.1 to 4 L/hr | 1.5 grams every 8 hours
4.1 L/hr or greater | 2 grams every 8 hours
CRRT = continuous renal replacement therapy.

Dosage Adjustments in Patients with CLcr 120 mL/min or Greater

For patients with CLcr greater than or equal to 120 mL/min, FETROJA 2 grams administered every 6 hours by IV infusion over 3 hours is recommended [see Use in Specific Populations (8.6)] .

2.3 Preparation of FETROJA Solution for Administration

FETROJA is supplied as a sterile, lyophilized powder that must be reconstituted and subsequently diluted using aseptic technique prior to intravenous infusion.

Preparation of Doses

Reconstitute the powder for injection in the FETROJA vial with 10 mL of either 0.9% sodium chloride injection, USP or 5% dextrose injection, USP and gently shake to dissolve. Allow the vial(s) to stand until the foaming generated on the surface has disappeared (typically within 2 minutes). The reconstituted solution will have a final volume of approximately 11.2 mL and concentration of 0.089 gram/mL. The reconstituted solution is for intravenous infusion only after dilution in an appropriate infusion solution.

To prepare the required doses, withdraw the appropriate volume of reconstituted solution from the vial according to Table 3 below. Add the withdrawn volume to a 100 mL infusion bag containing 0.9% sodium chloride injection, USP or 5% dextrose injection, USP [see Dosage and Administration (2.4)] .

Parenteral drug products should be inspected visually for particulate matter and discoloration prior to administration, whenever solution and container permit. FETROJA infusions are clear, colorless solutions. Discard any unused FETROJA solution in the vial (see Table 3).

Table 3 Preparation of FETROJA Doses
FETROJA Dose | Number of 1-gram FETROJA Vials to be Reconstituted | Volume to Withdraw from Reconstituted Vial(s) | Total Volume of FETROJA Reconstituted Solution for Further Dilution into a 100 mL Infusion Bag
2 grams | 2 vials | 11.2 mL (entire contents) of each vial | 22.4 mL
1.5 grams | 2 vials | 11.2 mL (entire contents) of first vial AND 5.6 mL from second vial | 16.8 mL
1 gram | 1 vial | 11.2 mL (entire contents) | 11.2 mL
0.75 gram | 1 vial | 8.4 mL | 8.4 mL

2.4 Drug Compatibility

FETROJA solution for administration is compatible with:

- 0.9% sodium chloride injection, USP
- 5% dextrose injection, USP

The compatibility of FETROJA solution for administration with solutions containing other drugs or other diluents has not been established.

2.5 Storage of Reconstituted Solutions

Reconstituted FETROJA

Upon reconstitution with the appropriate diluent, the reconstituted FETROJA solution in the vial should be immediately transferred and diluted into the infusion bag. Reconstituted FETROJA can be stored for up to 1 hour at room temperature in the vial. Discard any unused reconstituted solution.

Diluted FETROJA Infusion Solution

The diluted FETROJA infusion solution in the infusion bag is stable for up to 6 hours at room temperature.

The diluted FETROJA infusion solution in the infusion bag may also be refrigerated at 2°C to 8°C (36°F to 46°F) for up to 24 hours, protected from light; and then the infusion should be completed within 6 hours at room temperature.

3 DOSAGE FORMS AND STRENGTHS

FETROJA 1 gram for injection is supplied as a white to off-white, sterile, lyophilized powder for reconstitution in single-dose, clear glass vials; each vial contains 1 gram of cefiderocol.

4 CONTRAINDICATIONS

FETROJA is contraindicated in patients with a known history of severe hypersensitivity to cefiderocol or other beta-lactam antibacterial drugs, or any other component of FETROJA [see Warnings and Precautions (5.2)and Adverse Reactions (6.1)] .

5 WARNINGS AND PRECAUTIONS

5.1 Increase in All-Cause Mortality in Patients with Carbapenem-Resistant Gram-Negative Bacterial Infections

An increase in all-cause mortality was observed in patients treated with FETROJA as compared to best available therapy (BAT) in a multinational, randomized, open-label trial in critically ill patients with carbapenem-resistant Gram-negative bacterial infections (NCT02714595). Patients with nosocomial pneumonia, bloodstream infections, sepsis, or cUTI were included in the trial. BAT regimens varied according to local practices and consisted of 1 to 3 antibacterial drugs with activity against Gram-negative bacteria. Most of the BAT regimens contained colistin.

The increase in all-cause mortality occurred in patients treated for nosocomial pneumonia, bloodstream infections, or sepsis. The 28-Day all-cause mortality was higher in patients treated with FETROJA than in patients treated with BAT [25/101 (24.8%) vs. 9/49 (18.4%), treatment difference 6.4%, 95% CI (-8.6, 19.2)]. All-cause mortality remained higher in patients treated with FETROJA than in patients treated with BAT through Day 49 [34/101 (33.7%) vs. 10/49 (20.4%), treatment difference 13.3%, 95% CI (-2.5, 26.9)]. Generally, deaths were in patients with infections caused by Gram-negative organisms, including non-fermenters such as Acinetobacter baumanniicomplex, Stenotrophomonas maltophilia, and Pseudomonas aeruginosa, and were the result of worsening or complications of infection, or underlying comorbidities. The cause of the increase in mortality has not been established.

Closely monitor the clinical response to therapy in patients with cUTI and HABP/VABP.

5.2 Hypersensitivity Reactions

Serious and occasionally fatal hypersensitivity (anaphylactic) reactions and serious skin reactions have been reported in patients receiving beta-lactam antibacterial drugs. Hypersensitivity was observed in FETROJA-treated patients in clinical trials [see Adverse Reactions (6.1)] . These reactions are more likely to occur in individuals with a history of beta-lactam hypersensitivity and/or a history of sensitivity to multiple allergens. There have been reports of individuals with a history of penicillin hypersensitivity who have experienced severe reactions when treated with cephalosporins.

Before therapy with FETROJA is instituted, inquire about previous hypersensitivity reactions to cephalosporins, penicillins, or other beta-lactam antibacterial drugs. Discontinue FETROJA if an allergic reaction occurs.

5.3 Clostridioides difficile-associated Diarrhea (CDAD)

Clostridioides difficile-associated diarrhea (CDAD) has been reported for nearly all systemic antibacterial agents, including FETROJA. CDAD may range in severity from mild diarrhea to fatal colitis. Treatment with antibacterial agents alters the normal flora of the colon and may permit overgrowth of C. difficile.

C. difficileproduces toxins A and B, which contribute to the development of CDAD. Hypertoxin-producing strains of C. difficilecause increased morbidity and mortality, as these infections can be refractory to antimicrobial therapy and may require colectomy. CDAD must be considered in all patients who present with diarrhea following antibacterial use. Careful medical history is necessary because CDAD has been reported to occur more than 2 months after the administration of antibacterial agents.

If CDAD is suspected or confirmed, antibacterial drugs not directed against C. difficilemay need to be discontinued. Manage fluid and electrolyte levels as appropriate, supplement protein intake, monitor antibacterial treatment of C. difficile, and institute surgical evaluation as clinically indicated.

5.4 Seizures and Other Central Nervous System (CNS) Adverse Reactions

Cephalosporins, including FETROJA, have been implicated in triggering seizures [see Adverse Reactions (6.1)] . Nonconvulsive status epilepticus (NCSE), encephalopathy, coma, asterixis, neuromuscular excitability, and myoclonia have been reported with cephalosporins particularly in patients with a history of epilepsy and/or when recommended dosages of cephalosporins were exceeded due to renal impairment. Adjust FETROJA dosing based on creatinine clearance [see Dosage and Administration (2.2)] . Anticonvulsant therapy should be continued in patients with known seizure disorders. If CNS adverse reactions including seizures occur, patients should undergo a neurological evaluation to determine whether FETROJA should be discontinued.

5.5 Development of Drug-Resistant Bacteria

Prescribing FETROJA in the absence of a proven or strongly suspected bacterial infection or a prophylactic indication is unlikely to provide benefit to the patient and increases the risk of the development of drug-resistant bacteria [see Indications and Usage (1.3)] .

6 ADVERSE REACTIONS

The following serious adverse reactions are described in greater detail in the Warnings and Precautions section:

- Increase in All-Cause Mortality in Patients with Carbapenem-Resistant Gram-Negative Bacterial Infections [see Warnings and Precautions (5.1)]
- Hypersensitivity Reactions [see Warnings and Precautions (5.2)]
- Clostridioides difficile-associated Diarrhea (CDAD) [see Warnings and Precautions (5.3)]
- Seizures and Other Central Nervous System Adverse Reactions [see Warnings and Precautions (5.4)]

6.1 Clinical Trials Experience

Because clinical trials are conducted under widely varying conditions, adverse reaction rates observed in the clinical trials of a drug cannot be directly compared to rates in the clinical trials of another drug and may not reflect the rates observed in practice.

Complicated Urinary Tract Infections (cUTIs), Including Pyelonephritis

FETROJA was evaluated in an active-controlled, randomized clinical trial in patients with cUTI, including pyelonephritis (Trial 1). In this trial, 300 patients received FETROJA 2 grams every 8 hours infused over 1 hour (or a renally-adjusted dose), and 148 patients were treated with imipenem/cilastatin 1gram/1gram every 8 hours infused over 1 hour (or a renally-adjusted dose). The median age of treated patients across treatment arms was 65 years (range 18 to 93 years), with approximately 53% of patients aged greater than or equal to 65. Approximately 96% of patients were White, most were from Europe, and 55% were female. Patients across treatment arms received treatment for a median duration of 9 days.

Serious Adverse Reactions and Adverse Reactions Leading to Discontinuation

In Trial 1, a total of 14/300 (4.7%) cUTI patients treated with FETROJA and 12/148 (8.1%) of cUTI patients treated with imipenem/cilastatin experienced serious adverse reactions. One death (0.3%) occurred in 300 patients treated with FETROJA as compared to none treated with imipenem/cilastatin. Discontinuation of treatment due to any adverse reaction occurred in 5/300 (1.7%) of patients treated with FETROJA and 3/148 (2.0%) of patients treated with imipenem/cilastatin. Specific adverse reactions leading to treatment discontinuation in patients who received FETROJA included diarrhea (0.3%), drug hypersensitivity (0.3%), and increased hepatic enzymes (0.3%).

Common Adverse Reactions

Table 4 lists the most common selected adverse reactions occurring in ≥ 2% of cUTI patients receiving FETROJA in Trial 1.

Table 4 Selected Adverse Reactions Occurring in ≥ 2% of cUTI Patients Receiving FETROJA in Trial 1
Adverse Reaction | FETROJA [2 grams IV over 1 hour every 8 hours (with dosing adjustment based on renal function).] (N = 300) | Imipenem/Cilastatin [1 gram IV over 1 hour every 8 hours (with dosing adjustment based on renal function and body weight).] (N = 148)
Diarrhea | 4% | 6%
Infusion site reactions [Infusion site reactions include infusion site erythema, inflammation, pain, pruritis, injection site pain, and phlebitis.] | 4% | 5%
Constipation | 3% | 4%
Rash [Rash includes rash macular, rash maculopapular, erythema, skin irritation.] | 3% | < 1%
Candidiasis [Candidiasis includes oral or vulvovaginal candidiasis, candiduria.] | 2% | 3%
Cough | 2% | < 1%
Elevations in liver tests [Elevations in liver tests include alanine aminotransferase, aspartate aminotransferase, gamma-glutamyl transferase, blood alkaline phosphatase, hepatic enzyme increased.] | 2% | < 1%
Headache | 2% | 5%
Hypokalemia [Hypokalemia includes blood potassium decreased.] | 2% | 3%
Nausea | 2% | 4%
Vomiting | 2% | 1%
cUTI = complicated urinary tract infection.

Other Adverse Reactions of FETROJA in the cUTI Patients (Trial 1)

The following selected adverse reactions were reported in FETROJA-treated cUTI patients at a rate of less than 2% in Trial 1:

Blood and lymphatic disorders: thrombocytosis

Cardiac disorders: congestive heart failure, bradycardia, atrial fibrillation

Gastrointestinal disorders: abdominal pain, dry mouth, stomatitis

General system disorders: pyrexia, peripheral edema

Hepatobiliary disorders: cholelithiasis, cholecystitis, gallbladder pain

Immune system disorders: drug hypersensitivity

Infections and infestations: C. difficileinfection

Laboratory investigations: prolonged prothrombin time (PT) and prothrombin time international normalized ratio (PT-INR), red blood cells urine positive, creatine phosphokinase increase

Metabolism and nutrition disorders: decreased appetite, hypocalcemia, fluid overload

Nervous system disorders: dysgeusia, seizure

Respiratory, thoracic, and mediastinal disorders: dyspnea, pleural effusion

Skin and subcutaneous tissue disorders: pruritis

Psychiatric disorders: insomnia, restlessness

Hospital-acquired Bacterial Pneumonia and Ventilator-associated Bacterial Pneumonia (HABP/VABP)

FETROJA was evaluated in an active-controlled clinical trial in patients with HABP/VABP (Trial 2). In this trial, 148 patients received FETROJA 2 grams every 8 hours infused over 3 hours, and 150 patients received meropenem 2 grams every 8 hours infused over 3 hours. Doses of study treatments were adjusted based on renal function. The median age was 67 years, approximately 59% of patients were 65 years of age and older, 69% were male, and 68% were White. Overall, approximately 60% were ventilated at randomization, including 41% with VABP and 14% with ventilated HABP. The mean Acute Physiology And Chronic Health Evaluation (APACHE II) score was 16. All patients received empiric treatment for Gram-positive organisms with linezolid for at least 5 days.

Serious Adverse Reactions and Adverse Reactions Leading to Discontinuation

In Trial 2, serious adverse reactions occurred in 54/148 (36.5%) HABP/VABP patients treated with FETROJA and 45/150 (30%) of HABP/VABP patients treated with meropenem. Adverse reactions leading to death were reported in 39/148 (26.4%) patients treated with FETROJA and 35/150 (23.3%) patients treated with meropenem. Adverse reactions leading to discontinuation of treatment occurred in 12/148 (8.1%) of patients treated with FETROJA and 14/150 (9.3%) of patients treated with meropenem. The most common adverse reactions leading to discontinuation in both treatment groups were elevated liver tests.

Common Adverse Reactions

Table 5 lists the most common selected adverse reactions occurring in ≥ 4% of patients receiving FETROJA in the HABP/VABP trial.

Table 5 Selected Adverse Reactions Occurring in ≥ 4% of HABP/VABP Patients Receiving FETROJA in Trial 2
Adverse Reaction | FETROJA [2 grams IV over 3 hours every 8 hours (with dosing adjustment based on renal function).] N = 148 | Meropenem [2 grams IV over 3 hours every 8 hours (with dosing adjustment based on renal function).] N = 150
Elevations in liver tests [Elevations in liver tests include the following terms: aspartate aminotransferase increased, alanine aminotransferase increased, gamma-glutamyl transferase increased, liver function test increased, liver function test abnormal, hepatic enzyme increased, transaminases increased, hypertransaminesemia.] | 16% | 16%
Hypokalemia [Hypokalemia includes blood potassium decreased.] | 11% | 15%
Diarrhea | 9% | 9%
Hypomagnesemia | 5% | < 1%
Atrial fibrillation | 5% | 3%
HABP/VABP = hospital-acquired bacterial pneumonia/ventilator-associated bacterial pneumonia.

Other Adverse Reactions of FETROJA in HABP/VABP Patients in Trial 2

The following selected adverse reactions were reported in FETROJA-treated HABP/VABP patients at a rate of less than 4% in Trial 2:

Blood and lymphatic disorders: thrombocytopenia, thrombocytosis

Cardiac disorders: myocardial infarction, atrial flutter

Gastrointestinal disorders: nausea, vomiting, abdominal pain

Hepatobiliary disorders: cholecystitis, cholestasis

Infections and infestations: C. difficileinfection, oral candidiasis

Laboratory investigations: prolonged prothrombin time (PT) and prothrombin time international normalized ratio (PT-INR), activated partial thromboplastin time (aPTT)

Metabolism and nutrition disorders: hypocalcemia, hyperkalemia

Nervous system disorders: seizure

Renal and genitourinary disorders: acute interstitial nephritis

Respiratory, thoracic, and mediastinal disorders: cough

Skin and subcutaneous tissue disorders: rash including rash erythematous

6.2 Postmarketing Experience

The following adverse reactions have been identified during postapproval use of FETROJA. Because these reactions are reported voluntarily from a population of uncertain size, it is not always possible to reliably estimate their frequency or establish a causal relationship to drug exposure.

Blood and lymphatic system disorders: neutropenia

Renal and urinary disorders: chromaturia

7 DRUG INTERACTIONS

7.1 Drug/Laboratory Test Interactions

Cefiderocol may result in false-positive results in dipstick tests (urine protein, ketones, or occult blood). Use alternate clinical laboratory methods of testing to confirm positive tests.

8 USE IN SPECIFIC POPULATIONS

8.1 Pregnancy

Risk Summary

There are no available data on FETROJA use in pregnant women to evaluate for a drug-associated risk of major birth defects, miscarriage, or adverse maternal or fetal outcomes.

Available data from published prospective cohort studies, case series, and case reports over several decades with cephalosporin use in pregnant women have not established drug-associated risks of major birth defects, miscarriage, or adverse maternal or fetal outcomes (see Data) .

Developmental toxicity studies with cefiderocol administered during organogenesis to rats and mice showed no evidence of embryo-fetal toxicity, including drug-induced fetal malformations, at doses providing exposure levels 0.9 times (rats) or 1.3 times (mice) higher than the average observed in patients receiving the maximum recommended daily dose.

The estimated background risk of major birth defects and miscarriage for the indicated population is unknown. All pregnancies have a background risk of birth defect, loss, or other adverse outcomes. In the U.S. general population, the estimated background risk of major birth defects and miscarriage in clinically recognized pregnancies is 2% to 4% and 15% to 20%, respectively.

Data

Human Data

While available studies cannot definitively establish the absence of risk, published data from prospective cohort studies, case series, and case reports over several decades have not identified an association with cephalosporin use during pregnancy and major birth defects, miscarriage, or other adverse maternal or fetal outcomes. Available studies have methodologic limitations, including small sample size, retrospective data collection, and inconsistent comparator groups.

Animal Data

Developmental toxicity was not observed in rats at intravenous doses of up to 1000 mg/kg/day or mice at subcutaneous doses of up to 2000 mg/kg/day given during the period of organogenesis (gestation days 6-17 in rats and 6-15 in mice). No treatment-related malformations or reductions in fetal viability were observed. Mean plasma exposure (AUC) at these doses was approximately 0.9 times (rats) and 1.3 times (mice) the daily mean plasma exposure in patients that received 2 grams of cefiderocol infused intravenously every 8 hours.

In a pre- and postnatal development study, cefiderocol was administered intravenously at doses up to 1000 mg/kg/day to rats from Day 6 of pregnancy until weaning. No adverse effects on parturition, maternal function, or pre- and postnatal development and viability of the pups were observed.

In pregnant rats, cefiderocol-derived radioactivity was shown to cross the placenta, but the amount detected in fetuses was a small percentage (< 0.5%) of the dose.

8.2 Lactation

Risk Summary

It is not known whether cefiderocol is excreted into human milk; however, cefiderocol-derived radioactivity was detected in the milk of lactating rats that received the drug intravenously. When a drug is present in animal milk, it is likely that the drug will be present in human milk. No information is available on the effects of FETROJA on the breastfed infant or on milk production.

The developmental and health benefits of breastfeeding should be considered along with the mother's clinical need for FETROJA and any potential adverse effects on the breastfed child from FETROJA or from the underlying maternal condition.

Data

Cefiderocol-derived radioactivity was detected in milk following intravenous administration to lactating rats. The peak level in rat milk was approximately 6% of the peak plasma level.

8.4 Pediatric Use

Safety and effectiveness of FETROJA in pediatric patients younger than 18 years of age have not been established.

8.5 Geriatric Use

cUTI

Of the 300 patients treated with FETROJA in the cUTI trial, 158 (52.7%) were 65 years of age and older, and 67 (22.3%) were 75 years of age and older. No overall differences in safety or efficacy were observed between these patients and younger patients.

HABP/VABP

Of the 148 patients treated with FETROJA in the HABP/VABP trial, 83 (56.1%) were 65 years of age and older, and 40 (27%) were 75 years of age and older.

The incidence of adverse reactions in patients treated with FETROJA was similar in patients under 65 years of age as compared to older patients (65 years of age and older and 75 years of age and older). The incidence of adverse reactions in older patients (65 years of age and older and 75 years of age and older) was also similar between treatment groups.

Clinical cure rates at the Test-of-Cure visit (TOC) in FETROJA-treated adult patients younger than 65 years of age, 65 years of age to younger than 75 years of age, and 75 years of age and older were 60%, 77.5%, and 60%, respectively. In comparison, the clinical cure rates at the TOC visit in the meropenem-treated patients for each of these subgroups were 65.5%, 64.4%, and 70.5%, respectively. The observed all-cause mortality rates at Day 14 in the FETROJA-treated patients for each of these subgroups were 12.3%, 7.5%, and 17.5%, respectively. In comparison, in the meropenem-treated patients for each of these subgroups, they were 10.3%, 17.8%, and 9.1%, respectively.

cUTI and HABP/VABP

FETROJA is known to be substantially excreted by the kidney, and the risk of adverse reactions to this drug may be greater in patients with impaired renal function. Because elderly patients are more likely to have decreased renal function, care should be taken in dose selection, and it may be useful to monitor renal function. No dosage adjustment is required based on age. Dosage adjustment for elderly patients should be based on renal function [see Dosage and Administration (2.2), Use in Specific Populations (8.6), and Clinical Pharmacology (12.3)] .

8.6 Renal Impairment

Patients with CLcr 60 to 89 mL/min

No dosage adjustment of FETROJA is recommended in patients with CLcr 60 to 89 mL/min.

Patients with CLcr Less Than 60 mL/min Including Patients Receiving Intermittent HD

Dose adjustment is required in patients with CLcr less than 60 mL/min, and in patients who are receiving HD. In patients requiring HD, complete HD at the latest possible time before the start of cefiderocol dosing [see Dosage and Administration (2.2)and Clinical Pharmacology (12.3)] . Monitor renal function regularly and adjust the dosage of FETROJA accordingly as renal function may change during the course of therapy.

Patients Receiving CRRT

A total of 16 patients treated with FETROJA received CRRT in clinical trials. Dosage adjustment of FETROJA is required in patients receiving CRRT including CVVH, CVVHD, and CVVHDF. Dosage of FETROJA should be based on the effluent flow rate in patients receiving CRRT [see Dosage and Administration (2.2)and Clinical Pharmacology (12.3)]. While on CRRT, a patient's residual renal function may change. Improvements or reductions in residual renal function may warrant a change in FETROJA dosage.

Patients with CLcr 120 mL/min or Greater

CLcr 120 mL/min or greater may be seen in seriously ill patients, who are receiving intravenous fluid resuscitation. Dosage adjustment of FETROJA is required in patients with CLcr 120 mL/min or greater [see Dosage and Administration (2.2)and Clinical Pharmacology (12.3)]. Monitor renal function regularly and adjust the dosage of FETROJA accordingly as renal function may change during the course of therapy.

8.7 Hepatic Impairment

The effects of hepatic impairment on the pharmacokinetics of cefiderocol have not been evaluated. Hepatic impairment is not expected to alter the elimination of cefiderocol as hepatic metabolism/excretion represents a minor pathway of elimination for cefiderocol. Dosage adjustments are not necessary in patients with impaired hepatic function.

10 OVERDOSAGE

There is no information on clinical signs and symptoms associated with an overdose of FETROJA. Patients who receive doses greater than the recommended dose regimen and have unexpected adverse reactions possibly associated with FETROJA should be carefully observed and given supportive treatment, and discontinuation or interruption of treatment should be considered.

Approximately 60% of cefiderocol is removed by a 3- to 4-hour hemodialysis session [see Clinical Pharmacology (12.3)].

11 DESCRIPTION

FETROJA is a cephalosporin antibacterial drug product consisting of cefiderocol sulfate tosylate for intravenous infusion. Cefiderocol functions as a siderophore [see Microbiology (12.4)] .

The chemical name of cefiderocol sulfate tosylate is Tris[(6 R,7 R)-7-[(2 Z)-2-(2-amino-1,3-thiazol-4-yl)-2-{[(2-carboxypropan-2-yl)oxy]imino}acetamido]-3-({1-[2-(2-chloro-3,4-dihydroxybenzamido)ethyl]pyrrolidin-1-ium-1-yl}methyl)-8-oxo-5-thia-1-azabicyclo[4.2.0]oct-2-ene-2-carboxylate] tetrakis(4-methylbenzenesulfonate) monosulfate hydrate, and the molecular weight is 3043.50 (anhydrous). The molecular formula is 3C30H34ClN7O10S2∙4C7H8O3S∙H2SO4∙xH2O.

Figure 1 Chemical Structure of Cefiderocol Sulfate Tosylate

FETROJA for injection is a white to off-white, sterile, lyophilized powder formulated with 1 gram of cefiderocol (equivalent to 1.6 grams of cefiderocol sulfate tosylate), sucrose (900 mg), sodium chloride (216 mg), and sodium hydroxide to adjust pH. The sodium content is approximately 176 mg/vial. The pH of the reconstituted solution of 1 gram cefiderocol (1 vial) dissolved in 10 mL water is 5.2 to 5.8.

12 CLINICAL PHARMACOLOGY

12.1 Mechanism of Action

FETROJA is an antibacterial drug [see Microbiology (12.4)] .

12.2 Pharmacodynamics

The percent time of dosing interval that unbound plasma concentrations of cefiderocol exceed the minimum inhibitory concentration (MIC) against the infecting organism best correlates with antibacterial activity in neutropenic murine thigh and lung infection models with E. coli, K. pneumoniae, P. aeruginosa, A. baumannii, and S. maltophilia. Compared to a 1-hour infusion, a 3-hour infusion increased the percent time of dosing interval that unbound plasma concentrations of cefiderocol exceed the MIC. The in vivoanimal pneumonia studies showed that the antibacterial activity of cefiderocol was greater at the human equivalent dosing regimen of 3-hour infusion compared to that of 1-hour infusion.

Cardiac Electrophysiology

At doses 1 and 2 times the maximum recommended dosage, FETROJA does not prolong the QT interval to any clinically relevant extent.

12.3 Pharmacokinetics

Cefiderocol exposures (Cmaxand daily AUC) in cUTI patients, HABP/VABP patients, and healthy volunteers are summarized in Table 6. Cefiderocol Cmaxand AUC increased proportionally with dose.

Table 6 Cefiderocol Exposures Mean (±SD) in Patients and Healthy Volunteers with CLcr 60 mL/min or Greater
PK Parameters | cUTI Patients [After multiple (every 8 hours) FETROJA 2-gram doses infused over 3 hours or adjusted based on renal function.] (N = 21) | HABP/VABP Patients (N = 146) | Healthy Volunteers [After a single FETROJA 2-gram dose was infused over 3 hours.] (N = 43)
Cmax(mg/L) | 115 (±57) | 111 (±56) | 91.4 (±17.9)
AUC0-24 hr(mg∙hr/L) | 1944 (±1097) | 1773 (±990) | 1175 (±203)
Cmax= maximum concentration.
AUC0-24 hr= area under the concentration time curve from 0 to 24 hours.

Distribution

The geometric mean (±SD) cefiderocol volume of distribution was 18.0 (±3.36) L. Plasma protein binding, primarily to albumin, of cefiderocol is 40% to 60%.

Following a FETROJA 2-gram dose (or renal function equivalent dose) at steady state in patients with pneumonia requiring mechanical ventilation with a 3-hour infusion, the cefiderocol concentrations in epithelial lining fluid ranged from 3.1 to 20.7 mg/L and 7.2 to 15.9 mg/L at the end of infusion and at 2 hours after the end of infusion, respectively.

Elimination

Cefiderocol terminal elimination half-life is 2 to 3 hours. The geometric mean (±SD) cefiderocol clearance is estimated to be 5.18 (±0.89) L/hr.

Metabolism

Cefiderocol is minimally metabolized [less than 10% of a single radiolabeled cefiderocol dose of 1 gram (0.5 times the approved recommended dosage) infused over 1 hour].

Excretion

Cefiderocol is primarily excreted by the kidneys. After a single radiolabeled cefiderocol 1-gram (0.5 times the approved recommended dosage) dose infused over 1 hour, 98.6% of the total radioactivity was excreted in urine (90.6% unchanged) and 2.8% in feces.

Specific Populations

No clinically significant differences in the pharmacokinetics of cefiderocol were observed based on age (18 to 93 years of age), sex, or race. The effect of hepatic impairment on the pharmacokinetics of cefiderocol was not evaluated.

Patients with Renal Impairment

Approximately 60% of cefiderocol was removed by a 3- to 4-hour hemodialysis session.

Cefiderocol AUC fold changes in subjects with renal impairment compared to subjects with CLcr 90 to 119 mL/min are summarized in Table 7.

Table 7 Effect of Renal Impairment on the AUC of Cefiderocol [After a single FETROJA 1-gram dose (0.5 times the approved recommended dosage).]
CLcr (mL/min) | Cefiderocol AUC Geometric Mean Ratios (90% CI) [Compared to AUC in subjects with CLcr 90 to 119 mL/min (N = 12).]
60 to 89 (N = 6) | 1.37 (1.15, 1.62)
30 to 59 (N = 7) | 2.35 (2.00, 2.77)
15 to 29 (N = 4) | 3.21 (2.64, 3.91)
< 15 (N = 6) | 4.69 (3.95, 5.56)
CI = confidence interval.

Patients Receiving CRRT

In an in vitrostudy, effluent flow rate was the major determinant of cefiderocol clearance by CRRT. Variables examined included effluent flow rate, CRRT mode (CVVH or CVVHD), filter type and point of dilution (pre- or post-filter dilution). The effluent flow rate-based dosing recommendations in Table 2 are predicted to provide cefiderocol exposures similar to those achieved with a dose of 2 grams given every 8 hours in patients not receiving CRRT [see Dosage and Administration (2.2)] .

Patients with CLcr 120 mL/min or Greater

Increased cefiderocol clearance has been observed in patients with CLcr 120 mL/min or greater. A FETROJA 2-gram dose every 6 hours infused over 3 hours provided cefiderocol exposures comparable to those in patients with CLcr 90 to 119 mL/min [see Dosage and Administration (2.2)] .

Drug Interaction Studies

Clinical Studies

No clinically significant differences in the pharmacokinetics of furosemide (an organic anion transporter [OAT]1 and OAT3 substrate), metformin (an organic cation transporter [OCT]1, OCT2, and multidrug and toxin extrusion [MATE]2-K substrate), and rosuvastatin (an organic anion transporting polypeptide [OATP]1B3 substrate) were observed when coadministered with cefiderocol.

In Vitro Studies Where Drug Interaction Potential Was Not Further Evaluated Clinically

Cytochrome P450 (CYP) Enzymes: Cefiderocol is not an inhibitor of CYP1A2, CYP2B6, CYP2C8, CYP2C9, CYP2C19, CYP2D6, CYP2E1, or CYP3A4. Cefiderocol is not an inducer of CYP1A2, CYP2B6, or CYP3A4.

Transporter Systems: Cefiderocol is not an inhibitor of OATP1B1, MATE1, P-glycoprotein (P-gp), breast cancer resistance protein (BCRP), or bile salt export pump transporters. Cefiderocol is not a substrate of OAT1, OAT3, OCT2, MATE1, MATE2-K, P-gp, or BCRP.

12.4 Microbiology

Mechanism of Action

FETROJA is a cephalosporin antibacterial with activity against Gram-negative aerobic bacteria. Cefiderocol functions as a siderophore and binds to extracellular free (ferric) iron. In addition to passive diffusion via porin channels, cefiderocol is actively transported across the outer cell membrane of bacteria into the periplasmic space using the bacterial siderophore iron uptake mechanism. Cefiderocol exerts bactericidal action by inhibiting cell wall biosynthesis through binding to penicillin-binding proteins (PBPs).

Cefiderocol has no clinically relevant in vitroactivity against most Gram-positive bacteria and anaerobic bacteria.

Resistance

In vitro,MIC increases that may result in resistance to cefiderocol in Gram-negative bacteria have been associated with a combination of multiple beta-lactamases, modifications of PBPs, and mutations of transcriptional regulators that impact siderophore expression.

Cefiderocol does not cause induction of AmpC beta-lactamase in P. aeruginosaand E. cloacae. The frequency of resistance development in Gram-negative bacteria including carbapenemase producers exposed to cefiderocol at 10× minimum inhibitory concentration (MIC) ranged from 10^-6to < 10^-8.

Cross-resistance with other classes of antibacterial drugs has not been identified; therefore, isolates resistant to other antibacterial drugs may be susceptible to cefiderocol.

Cefiderocol has shown in vitroactivity against isolates of S. maltophiliaand a subset of isolates of Enterobacterales and P. aeruginosathat are resistant to meropenem, ciprofloxacin, amikacin, cefepime, ceftazidime-avibactam, and ceftolozane/tazobactam .Cefiderocol has shown in vitroactivity against subset of isolates of A. baumanniicomplex that are resistant to meropenem, ciprofloxacin, and amikacin .Cefiderocol is active against some colistin-resistant E. coliisolates containing mcr-1.

Cefiderocol demonstrated in vitroactivity against a subgroup of Enterobacterales genetically confirmed to contain the following: ESBLs (TEM, SHV, CTX-M, oxacillinase [OXA]), AmpC, AmpC-type ESBL (CMY), serine-carbapenemases (such as KPC, OXA-48), and metallo-carbapenemases (such as NDM and VIM). Cefiderocol demonstrated in vitroactivity against a subgroup of P. aeruginosagenetically confirmed to contain VIM, IMP, GES, AmpC, and a subgroup of A. baumanniicontaining OXA-23, OXA-24/40, OXA-51, OXA-58, and AmpC. Cefiderocol is active in vitroagainst a subgroup of S. maltophiliacontaining metallo-carbapenemase (L1) and serine beta-lactamases (L2).

Cefiderocol maintained in vitroactivity against K. pneumoniaein the presence of porin channel deletions (OmpK35/36), and against P. aeruginosain the presence of porin channel deletions (OprD) and efflux pump up-regulation (MexAB-OprM, MexCD-OprJ, MexEF-OprN, and MexXY).

In vitro,the addition of the beta-lactamase inhibitors (such as avibactam, clavulanic acid, and dipicolinic acid) results in the lowering of MICs of some clinical isolates with relatively high MICs (range 2 to 256 mcg/mL) to cefiderocol.

Interaction with Other Antimicrobials

In vitrostudies showed no antagonism between cefiderocol and amikacin, ceftazidime/avibactam, ceftolozane/tazobactam, ciprofloxacin, clindamycin, colistin, daptomycin, linezolid, meropenem, metronidazole, tigecycline, or vancomycin against strains of Enterobacterales, P. aeruginosa, and A. baumannii.

Activity against Bacteria in Animal Infection Models

In a neutropenic murine thigh infection model using a humanized dose (2 grams every 8 hours), cefiderocol demonstrated 1log10reduction in bacterial burden against most E. coli, K. pneumoniae, A. baumannii, S. maltophilia,and P. aeruginosaincluding some carbapenemase-producing (KPC, OXA-23, OXA-24/40, OXA-58) isolates with MICs of ≤ 4 mcg/mL to cefiderocol.

In an immunocompetent rat pneumonia model, reduction in bacterial counts in the lungs of animals infected with K. pneumoniaewith MICs ≤ 8 mcg/mL, A. baumanniiwith MICs ≤ 2 mcg/mL ,and P. aeruginosawith MICs ≤ 1 mcg/mL including carbapenemase-producing (KPC, NDM, and IMP) isolates was observed using humanized cefiderocol drug exposure.

In an immunocompetent murine urinary tract infection model, cefiderocol reduced bacterial counts in the kidneys of mice infected with E. coli, K. pneumoniae, and P. aeruginosaisolates with MICs ≤ 1 mcg/mL. In an immunocompromised murine systemic infection model, cefiderocol increased survival in mice infected with E. cloacae, S. maltophilia, and Burkholderia cepaciaisolates with MICs ≤ 0.5 mcg/mL compared to untreated mice. In an immunocompetent murine systemic infection model, cefiderocol increased survival in mice infected with S. marcescensand P. aeruginosaisolates with MICs ≤ 1 mcg/mL compared to untreated mice.

The clinical significance of the above findings in animal infection models is not known.

Antimicrobial Activity

FETROJA has been shown to be active against the following bacteria, both in vitroand in clinical infections [see Indications and Usage (1)] :

Complicated Urinary Tract Infections, Including Pyelonephritis

Gram-negative Bacteria

Escherichia coli

Enterobacter cloacaecomplex

Klebsiella pneumoniae

Proteus mirabilis

Pseudomonas aeruginosa

Hospital-acquired Bacterial Pneumonia and Ventilator-associated Bacterial Pneumonia (HABP/VABP)

Gram-negative Bacteria

Acinetobacter baumanniicomplex

Escherichia coli

Enterobacter cloacaecomplex

Klebsiella pneumoniae

Pseudomonas aeruginosa

Serratia marcescens

The following in vitrodata are available, but their clinical significance is not known. At least 90% of the following bacteria exhibit an in vitrominimum inhibitory concentration (MIC) less than or equal to the susceptible breakpoint for FETROJA against isolates of similar genus or organism group. However, the efficacy of FETROJA in treating clinical infections caused by these bacteria has not been established in adequate and well-controlled clinical trials.

Gram-negative Bacteria

Achromobacter spp.

Burkholderia cepaciacomplex

Citrobacter freundiicomplex

Citrobacter koseri

Klebsiella aerogenes

Klebsiella oxytoca

Morganella morganii

Proteus vulgaris

Providencia rettgeri

Stenotrophomonas maltophilia

Susceptibility Testing

For specific information regarding susceptibility test interpretive criteria and associated test methods and quality control standards recognized by FDA for this drug, please see https://www.fda.gov/STIC.

13 NONCLINICAL TOXICOLOGY

13.1 Carcinogenesis, Mutagenesis, Impairment of Fertility

Carcinogenesis

Carcinogenicity studies in animals have not been conducted with cefiderocol.

Mutagenesis

Cefiderocol was negative for genotoxicity in a reverse mutation test with S. typhimuriumand E. coliand did not induce mutations in V79 Chinese hamster lung cells. Cefiderocol was positive in a chromosomal aberration test in cultured TK6 human lymphoblasts and increased mutation frequency in L5178Y mouse lymphoma cells. Cefiderocol was negative in an in vivorat micronucleus test and a rat comet assay at the highest doses of 2000 and 1500 mg/kg/day, respectively.

Impairment of Fertility

Cefiderocol did not affect fertility in adult male or female rats when administered intravenously at doses up to 1000 mg/kg/day. The AUC at this dose is approximately 0.9 times the mean daily cefiderocol exposure in patients who received the maximum recommended clinical dose of 2 grams every 8 hours.

14 CLINICAL STUDIES

14.1 Complicated Urinary Tract Infections, Including Pyelonephritis

A total of 448 adults hospitalized with cUTI (including pyelonephritis) were randomized in a 2:1 ratio and received study medications in a multinational, double-blind trial (Trial 1) (NCT02321800) comparing FETROJA 2 grams intravenously (IV) every 8 hours (infused over 1 hour) to imipenem/cilastatin 1gram/1gram IV every 8 hours (infused over 1 hour) for 7 to 14 days. No switch from IV to oral antibacterial therapy was permitted.

Efficacy was assessed as a composite of microbiological eradication and clinical cure at the Test-of-Cure visit (TOC) in the microbiological intent-to-treat (Micro-ITT) population, which included all patients who received at least a single dose of study medication and had at least one baseline Gram-negative uropathogen. Other efficacy endpoints included the microbiological eradication rate and the clinical response rate at TOC in the Micro-ITT population.

The Micro-ITT population consisted of 371 patients of whom 25% had cUTI with pyelonephritis, 48% had cUTI without pyelonephritis, and 27% had acute uncomplicated pyelonephritis. Complicating conditions included obstructive uropathy, catheterization, and renal stones. The median age was 66 years, with 24% of patients over the age of 75 years, and 55% of the population were female. The median duration of therapy in both treatment groups was 9 days (range 1-14 days). Of the 371 patients, 32% had CLcr > 50-80 mL/min, 17% had CLcr 30-50 mL/min, and 3% had CLcr < 30 mL/min at baseline. Concomitant Gram-negative bacteremia was identified in 7% of patients. In the Micro-ITT population, the most common baseline pathogens were E. coliand K. pneumoniae.

Table 8 provides the results of a composite of microbiological eradication (all Gram-negative uropathogens found at baseline at ≥ 10^5CFU/mL reduced to < 10^4CFU/mL) and clinical response (resolution or improvement of cUTI symptoms and no new symptoms assessed by the investigator) at the TOC visit, 7+/-2 days after the last dose of study drug. The response rates for the composite endpoint of microbiological eradication and clinical response at the TOC visit were higher in the FETROJA arm compared with imipenem/cilastatin, as shown in Table 8. Clinical response rates at the TOC visit were similar between FETROJA and imipenem/cilastatin. Most patients with microbiological failure at the TOC visit in either treatment arm did not require further antibacterial drug treatment. Subgroup analyses examining composite outcomes by baseline pathogen are shown in Table 9 and demonstrated responses consistent with the overall population. Subgroup analyses examining outcomes by age, gender, and/or outcomes in patients with renal impairment, concomitant bacteremia, complicated UTI with or without pyelonephritis, or acute uncomplicated pyelonephritis demonstrated responses were consistent with the overall population.

Table 8 Composite, Microbiological, and Clinical Response Rates at the TOC Visit in cUTI Patients (Micro-ITT Population) in Trial 1
Study Endpoint | FETROJA n/N (%) | Imipenem/Cilastatin n/N (%) | Treatment Difference (95% CI) [The treatment difference and 95% CI were based on the Cochran-Mantel-Haenszel method.]
Composite response at TOC | 183/252 (72.6%) | 65/119 (54.6%) | 18.6 (8.2, 28.9)
Microbiologic response TOC | 184/252 (73.0%) | 67/119 (56.3%) | 17.3 (6.9, 27.6)
Clinical response TOC | 226/252 (89.7%) | 104/119 (87.4%) | 2.4 (-4.7, 9.4)
CI = confidence interval; Micro-ITT = microbiological intent-to-treat; TOC = Test of Cure.

Table 9 Composite Endpoint of Microbiological Eradication and Clinical Response at the TOC Visit in cUTI Patients (Micro-ITT Population) by Baseline Pathogen [Patients may have had more than one pathogen in the baseline urine culture.] Subgroups
Baseline Pathogen Subgroup | FETROJA n/N (%) | Imipenem/Cilastatin n/N (%)
Escherichia coli | 113/152 (74.3) | 45/79 (57.0)
Klebsiella pneumoniae | 36/48 (75.0) | 12/25 (48.0)
Proteus mirabilis | 13/17 (76.5) | 0/2 (0.0)
Pseudomonas aeruginosa | 8/18 (44.4) | 3/5 (60.0)
Enterobacter cloacaecomplex | 8/13 (61.5) | 3/3 (100.0)

In the FETROJA treatment group, 61 (24.2%) bacterial isolates were ESBL producers compared with 32 (26.9%) in the imipenem/cilastatin group. The composite response rate of patients with these ESBL isolates at the TOC visit was consistent with the overall results.

14.2 Hospital-acquired Bacterial Pneumonia and Ventilator-associated Bacterial Pneumonia (HABP/VABP)

A total of 298 hospitalized adults with HABP/VABP received study medications in a multicenter, randomized, double-blind trial (Trial 2) (NCT03032380) comparing FETROJA 2 grams administered intravenously every 8 hours as a 3-hour infusion to meropenem (2 grams every 8 hours infused over 3 hours). Dosing was adjusted for renal function. Patients in both treatment arms received linezolid 600 mg every 12 hours for at least 5 days for empiric treatment of Gram-positive organisms. The trial protocol permitted administration of potentially active prior antibacterial therapy for no more than 24 hours within 72 hours prior to randomization and disallowed systemic concomitant antibacterial therapy until the Test-of-Cure visit (TOC, 7 days after end of treatment). The analysis population was the modified intent-to-treat (mITT) population, which included all randomized patients who received study medication and had evidence of bacterial pneumonia, except those with only anaerobic or Gram-positive aerobic infections.

Of the 292 patients in the mITT population, the median age was 67 years, and 58% of the population was 65 years of age and older, with 29% of the population 75 years of age and older. The majority of patients were male (68%), White (69%), and were from Europe (67%). Approximately 4% (11/292) were from the United States. The median baseline APACHE II score was 15, and 29% of patients had a baseline APACHE II score of greater than or equal to 20. At randomization, 68% of patients were in the ICU, and 60% were mechanically ventilated. 60% of patients had CLcr less than or equal to 80 mL/min at baseline; among these, 34% had CLcr less than or equal to 50 mL/min, and 14% had a CLcr less than 30 mL/min. Augmented renal clearance (CLcr greater than 120 mL/min) was present in 16% of patients. Gram-negative bacteremia was present at baseline in 6% of patients. In both treatment groups, most patients (70%) received between 7 and 14 days of study medication and 18% between 15 and 21 days.

Table 10 shows the Day 14 and Day 28 all-cause mortality rates, as well as clinical cure at the TOC visit. FETROJA was noninferior to meropenem with regard to the primary efficacy endpoint (Day 14 all-cause mortality in the mITT population). Clinical cure was defined as resolution or substantial improvement in signs and symptoms associated with pneumonia, such that no additional antibacterial therapy was required for the treatment of the current infection through the TOC visit.

Table 10 All-cause Mortality and Clinical Cure at the TOC Visit in HABP/VABP Patients (mITT Population) in Trial 2
Endpoint | FETROJA n/N (%) | Meropenem n/N (%) | Treatment Difference [The adjusted treatment difference (FETROJA minus meropenem) and associated 95% CI were based on the Cochran-Mantel-Haenszel stratum-weighted method. Subjects with unknown survival status were considered deaths. For Day 14 All-cause Mortality, 1 meropenem subject had unknown status; for Day 28 All-cause Mortality, 1 meropenem subject and 2 FETROJA subjects had unknown status.] (95% CI)
Day 14 All-cause Mortality | 18/145 (12.4) | 18/147 (12.2) | 0.2 (-7.2, 7.7)
Day 28 All-cause Mortality | 32/145 (22.1) | 31/147 (21.1) | 1.1 (-8.2, 10.4)
Clinical Cure at TOC | 94/145 (64.8) | 98/147 (66.7) | -2.0 (-12.5, 8.5)
CI = confidence interval; TOC = Test of Cure.

The Day 14 and Day 28 all-cause mortality rates by pathogen in patients in the mITT population who had a baseline LRT pathogen that was susceptible to meropenem are shown in Table 11; the clinical outcome at the TOC visit is shown in Table 12. There were 51 patients with A. baumanniicomplex at baseline, of which 17 (33.3%) patients had isolates susceptible to meropenem (MIC ≤ 8 mcg/mL, based on meropenem 2 grams every 8 hours). Among 51 patients with A. baumanniicomplex at baseline, all-cause mortality at Day 14 was 5/26 (19.2%) in FETROJA and 4/25 (16.0%) in the meropenem treatment group and at Day 28 was 9/26 (34.6%) in FETROJA and 6/25 (24.0%) in the meropenem treatment group. The clinical cure rates at the TOC visit were 14/26 (53.8%) in the FETROJA and 15/25 (60.0%) in the meropenem treatment group.

Table 11 All-cause Mortality by Baseline Pathogens Susceptible to Meropenem [Susceptible defined as MIC of ≤ 8 mcg/mL to meropenem.] in HABP/VABP Patients (mITT Population) in Trial 2
Baseline Pathogen | Day 14 All-cause Mortality |  | Day 28 All-cause Mortality
Baseline Pathogen | FETROJA n/N (%) | Meropenem n/N (%) | FETROJA n/N (%) | Meropenem n/N (%)
Klebsiella pneumoniae | 4/38 (10.5) | 4/36 (11.1) | 8/38 (21.1) | 9/36 (25.0)
Pseudomonas aeruginosa | 2/20 (10.0) | 4/17 (23.5) | 2/20 (10.0) | 5/17 (29.4)
Acinetobacter baumanniicomplex [Includes A. baumannii, A. nosocomialis, and A. pittii.] | 1/8 (12.5) | 0/9 (0.0) | 3/8 (37.5) | 0/9 (0.0)
Escherichia coli | 3/18 (16.7) | 3/21 (14.3) | 5/18 (27.8) | 4/21 (19.0)
Other Enterobacterales [Includes Enterobacter cloacae complex (E. cloacae, E. asburiae, and E. kobei) and Serratia marcescens.] | 2/16 (12.5) | 2/14 (14.3) | 4/16 (25.0) | 3/14 (21.4)
Each cell excludes subjects in whom baseline pathogen had meropenem MIC > 8 mcg/mL or where MIC was unknown.
Subjects with unknown survival status were considered deaths.

Table 12 Clinical Cure Rates by Baseline Pathogen Susceptible to Meropenem [Susceptible defined as MIC of ≤ 8 mcg/mL to meropenem.] at the TOC Visit in HABP/VABP (mITT Population) in Trial 2
Baseline Pathogen | Clinical Cure
Baseline Pathogen | FETROJA n/N (%) | Meropenem n/N (%)
Klebsiella pneumoniae | 24/38 (63.2) | 23/36 (63.9)
Pseudomonas aeruginosa | 13/20 (65.0) | 13/17 (76.5)
Acinetobacter baumanniicomplex [Includes A. baumannii, A. nosocomialis, and A. pittii.] | 6/8 (75.0) | 7/9 (77.8)
Escherichia coli | 12/18 (66.7) | 13/21 (61.9)
Other Enterobacterales [Includes Enterobacter cloacae complex (E. cloacae, E. asburiae, and E. kobei) and Serratia marcescens.] | 10/16 (62.5) | 8/14 (57.1)
Each cell excludes subjects whose pathogen-specific meropenem MIC was > 8 mcg/mL or where MIC was unknown.

In the FETROJA treatment group, 45 (31%) patients had ESBL-producing bacterial isolates compared with 42 (28.6%) patients in the meropenem treatment group. All-cause mortality at Day 14 and Day 28 of patients with these ESBL-producing bacterial isolates was consistent with the overall results.

16 HOW SUPPLIED/STORAGE AND HANDLING

16.1 How Supplied

FETROJA 1 gram (cefiderocol) for injection is supplied as a white to off-white sterile lyophilized powder for reconstitution in single-dose, clear glass vials (NDC 59630-266-01) sealed with a rubber stopper (not made with natural rubber latex) and an aluminum seal with flip-off cap. Each vial is supplied in cartons containing 10 single-dose vials.

 | NDC 59630-266-10 | FETROJA (cefiderocol) 1 gram/vial, 10 vials/carton

16.2 Storage and Handling

FETROJA vials should be stored refrigerated at 2°C to 8°C (36°F to 46°F). Protect from light. Store in the carton until time of use. Store reconstituted solutions of FETROJA at room temperature [see Dosage and Administration (2.5)] .

17 PATIENT COUNSELING INFORMATION

Serious Allergic Reactions

Advise patients and their families that allergic reactions, including serious allergic reactions, could occur with FETROJA and that serious reactions require immediate treatment. Ask patients about any previous hypersensitivity reactions to FETROJA, other beta-lactams (including cephalosporins), or other allergens [see Warnings and Precautions (5.2)] .

Potentially Serious Diarrhea

Advise patients and their families that diarrhea is a common problem caused by antibacterial drugs, including FETROJA. Sometimes, frequent watery or bloody diarrhea may occur and may be a sign of a more serious intestinal infection. If severe watery or bloody diarrhea develops, tell patient to contact his or her healthcare provider [see Warnings and Precautions (5.3)] .

Seizures

Counsel patients on the implication of cephalosporins, including FETROJA, in triggering seizures, particularly in patients with renal impairment when the dosage was not reduced and in patients with a history of epilepsy [see Warnings and Precautions (5.4)] .

Antibacterial Resistance

Patients should be counseled that antibacterial drugs including FETROJA should only be used to treat bacterial infections. They do not treat viral infections (e.g., influenza, common cold). When FETROJA is prescribed to treat a bacterial infection, patients should be told that although it is common to feel better early in the course of therapy, the medication should be taken exactly as directed. Skipping doses or not completing the full course of therapy may (1) decrease the effectiveness of the immediate treatment and (2) increase the likelihood that bacteria will develop resistance and will not be treatable by FETROJA or other antibacterial drugs in the future [see Warnings and Precautions (5.5)] .

Manufactured by
Shionogi & Co., Ltd.
Osaka 541-0045
Japan

Manufactured for
Shionogi Inc.
Florham Park, NJ
USA, 07932

PRINCIPAL DISPLAY PANEL - 1 Gram Vial Carton

Rx ONLY
NDC 59630-266-10

1 gram

Fetroja®
(cefiderocol) for injection
1 gram per vial

For Intravenous Infusion.
Must be reconstituted then diluted.
Contains 10 single-dose vials.

SHIONOGI